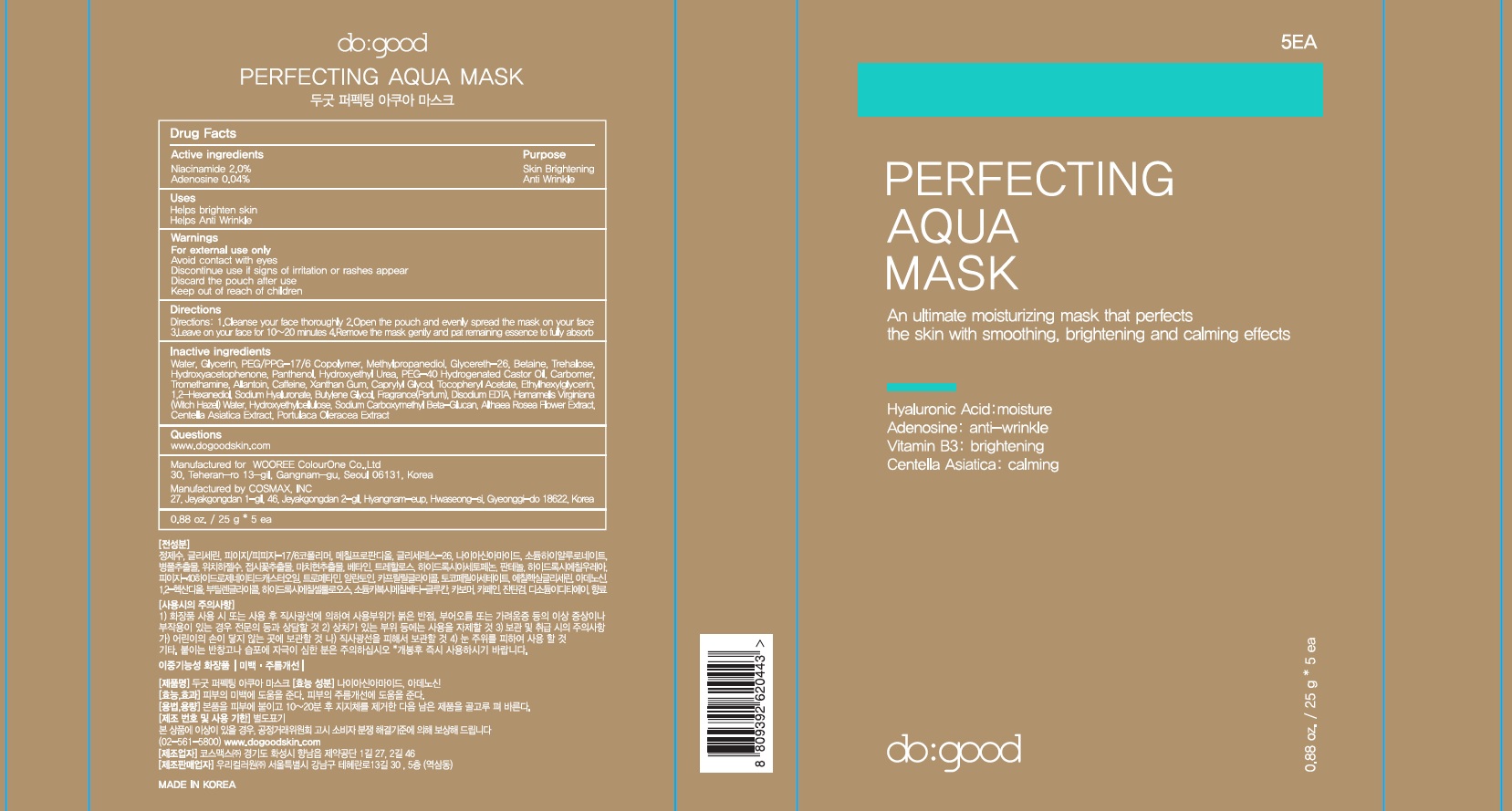 DRUG LABEL: do good Perfecting Aqua Mask
NDC: 72058-030 | Form: PATCH
Manufacturer: WOOREE Colourone Co.,Ltd
Category: otc | Type: HUMAN OTC DRUG LABEL
Date: 20180205

ACTIVE INGREDIENTS: Niacinamide 0.5 g/25 g; Adenosine 0.01 g/25 g
INACTIVE INGREDIENTS: Water; Glycerin

ACTIVE INGREDIENT

Active Ingredients: Niacinamide 2.0%, Adenosine 0.04%

INACTIVE INGREDIENT

Inactive Ingredients: Water, Glycerin, PEG/PPG-17/6 Copolymer, Methylpropanediol, Glycereth-26, Sodium Hyaluronate, Centella Asiatica Extract, Hamamelis Virginiana (Witch Hazel) Water, Althaea Rosea Flower Extract, Portulaca Oleracea Extract, Betaine, Trehalose, Hydroxyacetophenone, Panthenol, Hydroxyethyl Urea, PEG-40 Hydrogenated Castor Oil, Tromethamine, Allantoin, Caprylyl Glycol, Tocopheryl Acetate, Ethylhexylglycerin, 1,2-Hexanediol, Butylene Glycol, Hydroxyethylcellulose, Sodium Carboxymethyl Beta-Glucan, Carbomer, Caffeine, Xanthan Gum, Fragrance(Parfum)

PURPOSE

Purpose: Skin Brightening, Anti Wrinkle

WARNINGS

Warnings: For external use only. Avoid contact with eyes. Discontinue use if signs of irritation or rashes appear. Discard the pouch after use. Keep out of reach of children.

KEEP OUT OF REACH OF CHILDREN

Uses

- Helps brighten skin

- Helps Anti Wrinkle

Directions

Directions: 1. Cleanse your face thoroughly 2. Open the pouch and evenly spread the mask on your face. 3. Leave on your face for 10~20 minutes. 4. Remove the mask gently and pat remaining essence to fully absorb

QUESTIONS

Questions: www.dogoodskin.com